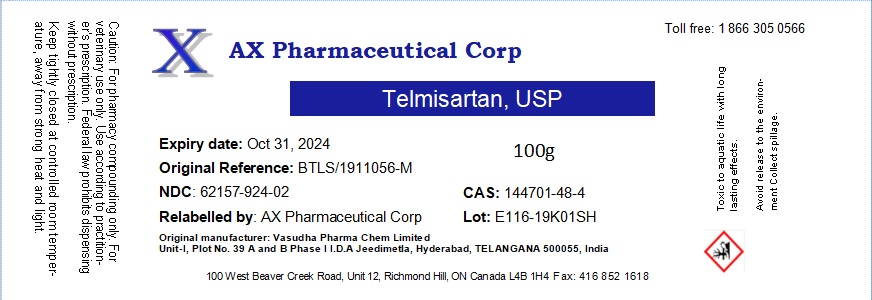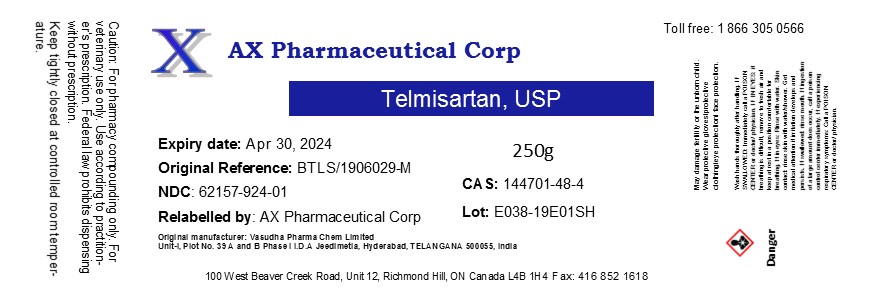 DRUG LABEL: Telmisartan
NDC: 62157-924 | Form: POWDER
Manufacturer: AX Pharmaceutical Corp
Category: other | Type: BULK INGREDIENT
Date: 20191023

ACTIVE INGREDIENTS: TELMISARTAN 1 g/1 g

Telmisartan